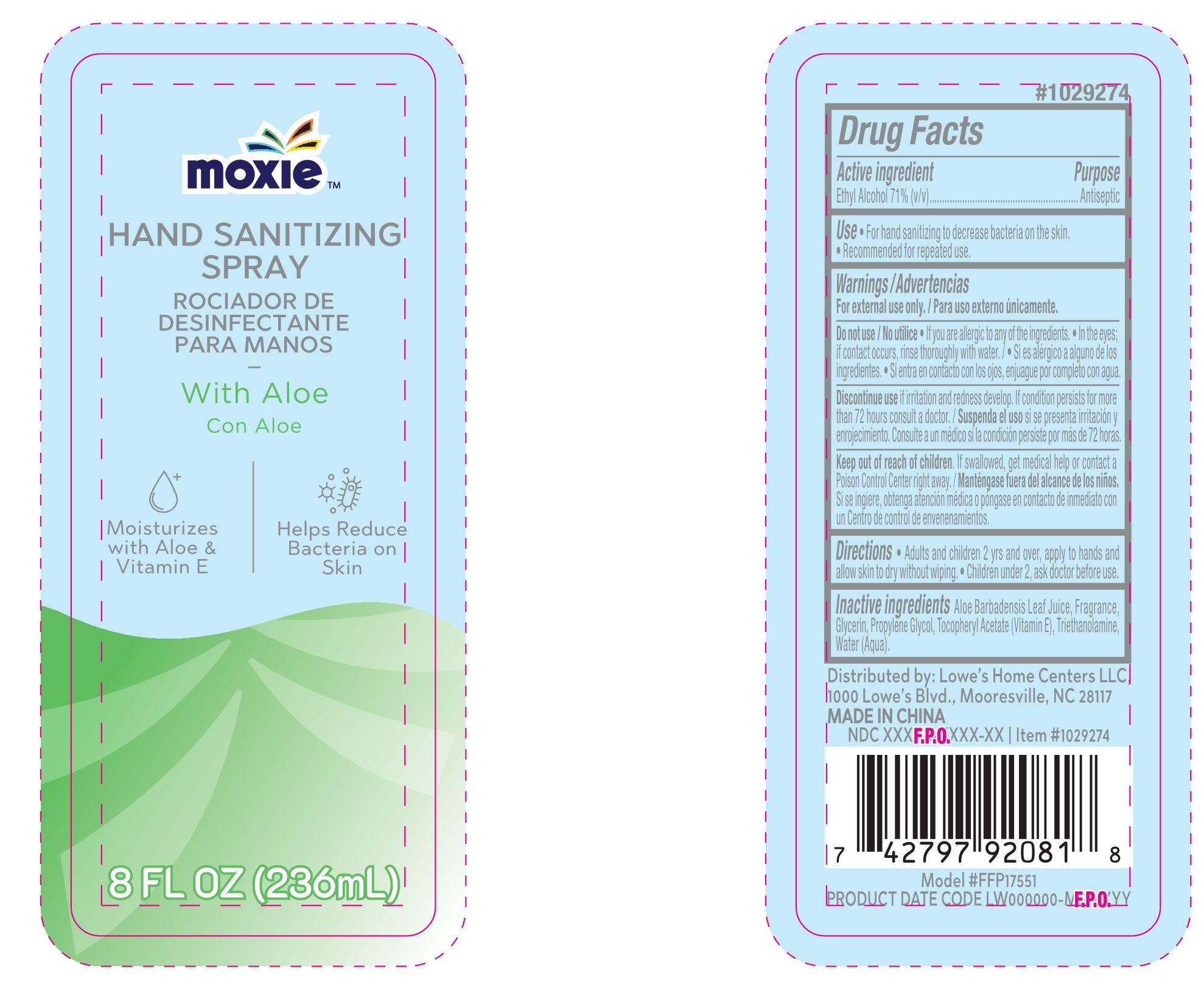 DRUG LABEL: HAND SANITIZER
NDC: 77720-018 | Form: SPRAY
Manufacturer: Skaffles Group Limited Liability Company
Category: otc | Type: HUMAN OTC DRUG LABEL
Date: 20201230

ACTIVE INGREDIENTS: ALCOHOL 71 mL/100 mL
INACTIVE INGREDIENTS: GLYCERIN; PROPYLENE GLYCOL; ALOE VERA LEAF; WATER; TROLAMINE; ALPHA-TOCOPHEROL ACETATE

77720-018 hand sanitizer Spray 71% Ethyl Alcohol

Active Ingredient

Ethyl Alcohol 71%

Purpose

Antiseptic

USE

Hand sanitizing to help reduce bacteria on the skin. Recommended for repeated use.

Warning

For external use only./ Para uso externo uinicamente.
Do not use / No utilice o lf you are allergic to any of the ingredients. o In the eyes;if contact occurs, rinse thoroughly with water.i Si es alergico a alguno de losingredientes.· Si entra en contacto con los ojos,enjuague por completo con agua.Discontinue use ifiritation and redness develop. lf condition persists for morethan 72 hours consult a doctor./Suspenda el uso si se presenta irritacion yenrojecimiento.Consulte a un medico si la condicion persiste por mas de 72 horas.Keep out of reach of children. If swallowed, get medical help or contact aPoison Control Center right away./ Mantengase fuera del alcance de los niios.Sise ingiere, obtenga atencion medica o pongase en contacto de inmediato conun Centro de control de envenenamientos.

Keep out of reach of children. If swallowed, get medical
help or contact a Poison Control Center right away.

Directions

Adtults and children 2 yrs and over, apply to hands and allow skin to dry without wiping. Children under 2, ask doctor before use.

Inactive ingredients

Aloe Barbadensis Leaf Juice, Fragrance, Glycerin, Propylene Glycol, TocopheryI Acetate (Vitamin E), Triethanolamine, Water(Aqua).